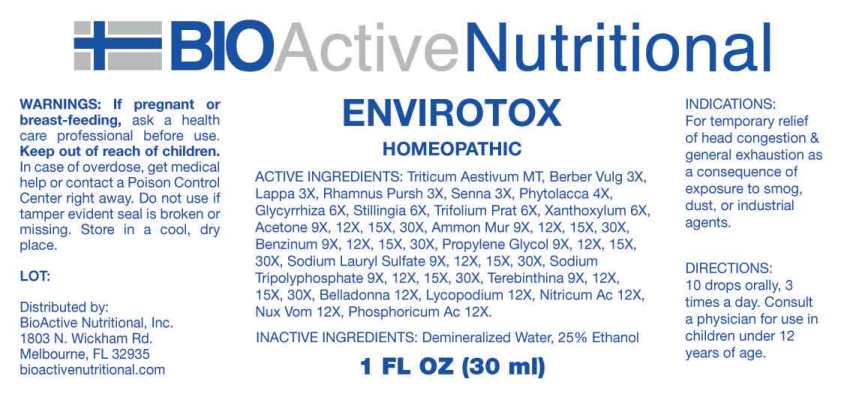 DRUG LABEL: Envirotox
NDC: 43857-0625 | Form: LIQUID
Manufacturer: BioActive Nutritional, Inc.
Category: homeopathic | Type: HUMAN OTC DRUG LABEL
Date: 20240326

ACTIVE INGREDIENTS: TRITICUM AESTIVUM WHOLE 1 [hp_X]/1 mL; BERBERIS VULGARIS ROOT BARK 3 [hp_X]/1 mL; ARCTIUM LAPPA ROOT 3 [hp_X]/1 mL; FRANGULA PURSHIANA BARK 3 [hp_X]/1 mL; SENNA LEAF 3 [hp_X]/1 mL; PHYTOLACCA AMERICANA ROOT 4 [hp_X]/1 mL; GLYCYRRHIZA GLABRA 6 [hp_X]/1 mL; STILLINGIA SYLVATICA ROOT 6 [hp_X]/1 mL; TRIFOLIUM PRATENSE FLOWER 6 [hp_X]/1 mL; ZANTHOXYLUM AMERICANUM BARK 6 [hp_X]/1 mL; ACETONE 9 [hp_X]/1 mL; SODIUM TRIPOLYPHOSPHATE, UNSPECIFIED FORM 9 [hp_X]/1 mL; PROPYLENE GLYCOL 9 [hp_X]/1 mL; BENZENE 9 [hp_X]/1 mL; AMMONIUM CHLORIDE 9 [hp_X]/1 mL; SODIUM LAURYL SULFATE 9 [hp_X]/1 mL; TURPENTINE OIL 9 [hp_X]/1 mL; ATROPA BELLADONNA WHOLE 12 [hp_X]/1 mL; LYCOPODIUM CLAVATUM SPORE 12 [hp_X]/1 mL; NITRIC ACID 12 [hp_X]/1 mL; STRYCHNOS NUX-VOMICA SEED 12 [hp_X]/1 mL; PHOSPHORIC ACID 12 [hp_X]/1 mL
INACTIVE INGREDIENTS: WATER; ALCOHOL

DRUG FACTS:

ACTIVE INGREDIENTS:

Triticum Aestivum 1X, Berberis Vulgaris 3X, Lappa Major 3X, Rhamnus Purshiana 3X, Senna (Cassia Angustifolia) 3X, Phytolacca Decandra 4X, Glycyrrhiza Glabra 6X, Stillingia Sylvatica 6X, Trifolium Pratense 6X, Xanthoxylum Fraxineum 6X, Acetonum Acetone 9X, 12X, 15X, 30X, Sodium Tripolyphosphate 9X, 12X, 15X, 30X, Propylene Glycol 9X, 12X, 15X, 30X, Benzinum 9X, 12X, 15X, 30X, Ammonium Muriaticum 9X, 12X, 15X, 30X, Sodium Lauryl Sulfate 9X, 12X, 15X, 30X, Terebinthina 9X, 12X, 15X, 30X, Belladonna 12X, Lycopodium Clavatum 12X, Nitricum Acidum 12X, Nux Vomica 12X, Phosphoricum Acidum 12X.

INDICATIONS:

For temporary relief of head congestion & general exhaustion as a consequence of exposure to smog, dust, or industrial agents.

WARNINGS:

If pregnant or breast-feeding, ask a health care professional before use.

Keep out of reach of children. In case of overdose, get medical help or contact a Poison Control Center right away.

Do not use if tamper evident seal is broken or missing.

Store in cool, dry place.

KEEP OUT OF REACH OF CHILDREN:

In case of overdose, get medical help or contact a Poison Control Center right away.

DIRECTIONS:

10 drops orally, 3 times a day. Consult a physician for use in children under 12 years of age.

INDICATIONS:

For temporary relief of head congestion & general exhaustion as a consequence of exposure to smog, dust, or industrial agents.

INACTIVE INGREDIENTS:

Demineralized Water, 25% Ethanol.

QUESTIONS:

Distributed by:
BioActive Nutritional, Inc.
1803 N. Wickham Rd.
Melbourne, FL 32935
bioactivenutritional.com

PACKAGE LABEL DISPLAY:

BIOActive Nutritional

ENVIROTOX

HOMEOPATHIC

1 FL OZ (30 ml)